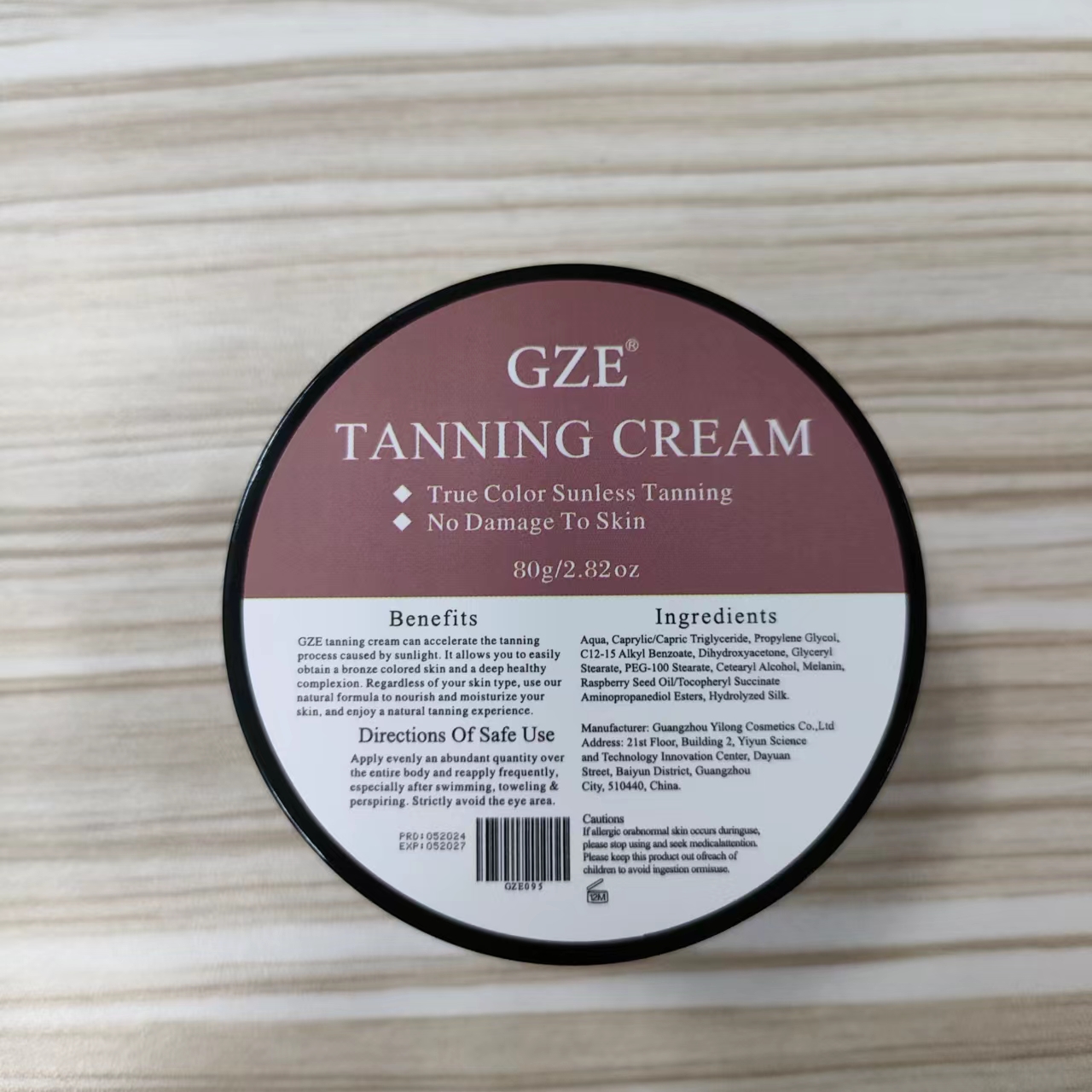 DRUG LABEL: GZE Tanning Cream
NDC: 74458-095 | Form: CREAM
Manufacturer: Guangzhou Yilong Cosmetics Co., Ltd
Category: otc | Type: HUMAN OTC DRUG LABEL
Date: 20241027

ACTIVE INGREDIENTS: DIHYDROXYACETONE 10 g/100 g
INACTIVE INGREDIENTS: RASPBERRY SEED OIL; PROPYLENE GLYCOL; GLYCERYL STEARATE; SILK, BASE HYDROLYZED (1000 MW); BLACK MARLIN; AQUA; CAPRYLIC/CAPRIC TRIGLYCERIDE; C12-15 ALKYL BENZOATE; CETEARYL ALCOHOL; PEG-100 STEARATE

GZE TANNING CREAM

ACTIVE INGREDIENT

Dihydroxyacetone

INACTIVE INGREDIENT

Aqua

Caprylic/Capric Triglyceride

Propylene Glycol

C12-15 Alkyl Benzoate

Glyceryl Stearate

PEG-100 Stearate

Cetearyl Alcohol

Melanin

Raspberry Seed Oil/Tocopheryl Succinate Aminopropanediol Esters

Hydrolyzed Silk

INDICATIONS AND USAGE

Apply evenly an abundant quantity over the entire body and reapply frequently,especially after swimming, toweling & perspiring. Strictly avoid the eye area.

PURPOSE

Sunless Tanning.

WARNINGS

For external use only.

Stop use and ask a doctor if rash occurs.

Do not use on damaged or broken skin.

When using this product keep out of eyes. Rinse with water to remove.

Keep out of reach of children. If swallowed, get medical help or contact a Poison Control Center right away.

DOSAGE AND ADMINISTRATION

Apply evenly an abundant quantity over the entire body and reapply frequently,especially after swimming, toweling &perspiring. Strictly avoid the eye area.